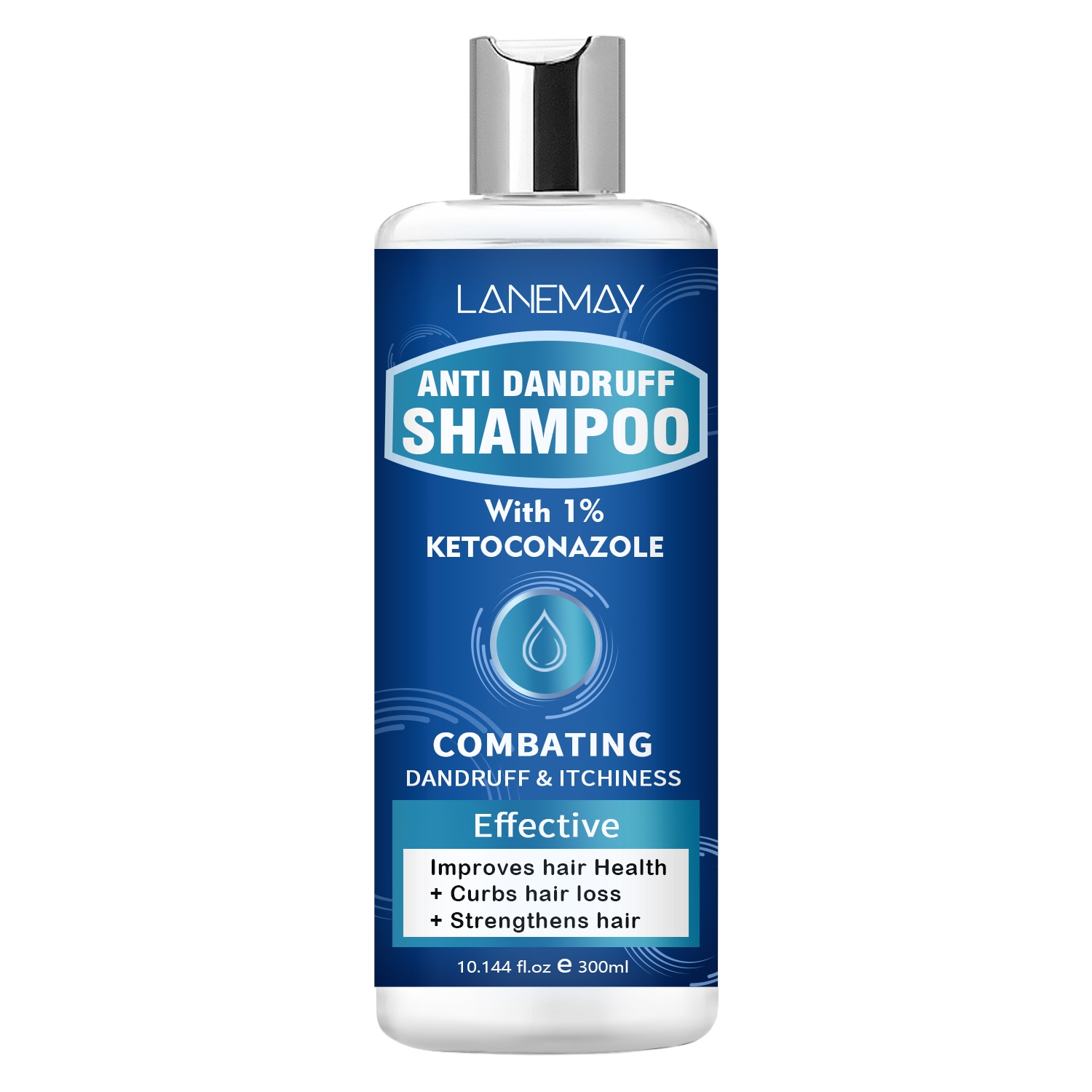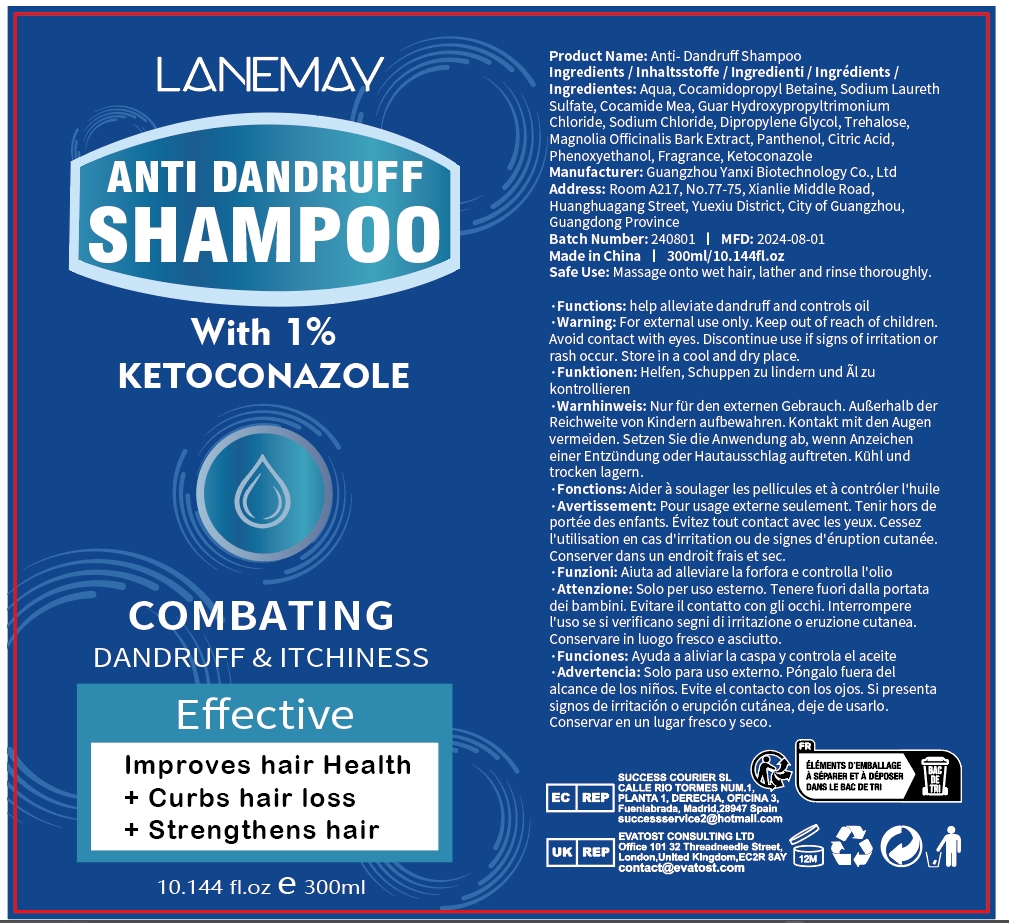 DRUG LABEL: Anti-DandruffShampoo
NDC: 84025-248 | Form: GEL
Manufacturer: Guangzhou Yanxi Biotechnology Co., Ltd
Category: otc | Type: HUMAN OTC DRUG LABEL
Date: 20241106

ACTIVE INGREDIENTS: COCAMIDOPROPYL BETAINE 15 mg/300 mL; COCAMIDE MEA 13 mg/300 mL
INACTIVE INGREDIENTS: WATER

DOSAGE AND ADMINISTRATION

Massage onto wet hair, lather and rinse thoroughly

WARNINGS

Keep out of children

INACTIVE INGREDIENT

Aqua

INDICATIONS AND USAGE

For daily hair care

Keep out of children

PURPOSE

help alleviate dandruffand controls oil